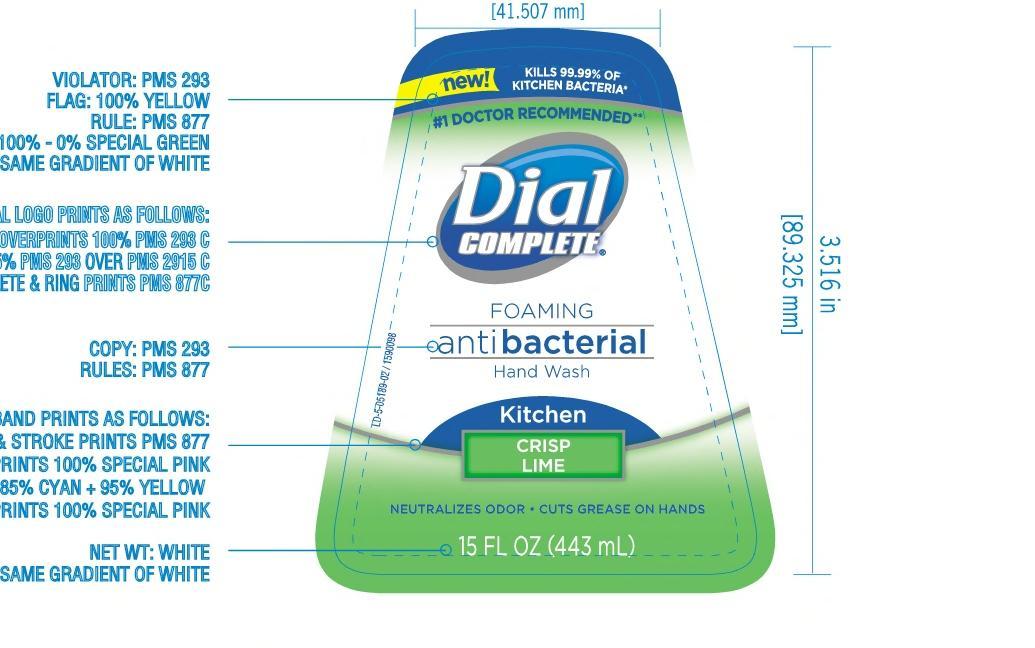 DRUG LABEL: Dial Complete Antibacterial Foaming Hand Washkitchen crisp limkitchen crisp lim
NDC: 54340-813 | Form: SOLUTION
Manufacturer: The Dial Corporation
Category: otc | Type: HUMAN OTC DRUG LABEL
Date: 20130312

ACTIVE INGREDIENTS: TRICLOSAN 0.46 mg/1000 mL
INACTIVE INGREDIENTS: WATER; SODIUM XYLENESULFONATE; DIPROPYLENE GLYCOL; GLYCERIN; SODIUM PYRROLIDONE CARBOXYLATE; AMMONIUM LAURYL SULFATE; COCAMIDOPROPYL BETAINE; POLYQUATERNIUM-10 (400 MPA.S AT 2%); SODIUM PHOSPHATE, DIBASIC, ANHYDROUS; CETYL ALCOHOL; ALOE VERA LEAF; CITRIC ACID MONOHYDRATE; METHYLPARABEN; PROPYLPARABEN; FD&C YELLOW NO. 5; D&C GREEN NO. 5

Drug Facts

Active Ingredient - TRICLOSAN 0.46%

PURPOSE

Antibacterial

INDICATIONS AND USAGE

For hand washing to decrease bacteria on the skin

WARNINGS

For external use only.

Stop use and ask a doctor if irritation and redness develops.

When using this product avoid contact with eyes. In case of eye contact, flush with water.

Keep out of reach of children. If swallowed, get medical help or contact a Poison Control Center right away.

DOSAGE AND ADMINISTRATION

Directions: Pump into dry hands. Lather vigorously for 15 seconds. Rinse and dry thoroughly.

INACTIVE INGREDIENT

Inactive Ingredients: Water, Sodium Xylenesulfonate, Dipropylene Glycol, Glycerin, Sodium PCA, Ammonium Lauryl Sulfate, Cocamidopropyl Betaine, Polyquaternium-10, Fragrance, Disodium Phosphate, Cetyl Alcohol, Aloe Barbadensis Leaf juice, Citric Acid, Methylparaben, Propylparaben

Questions? 1-800-258-DIAL

Label image